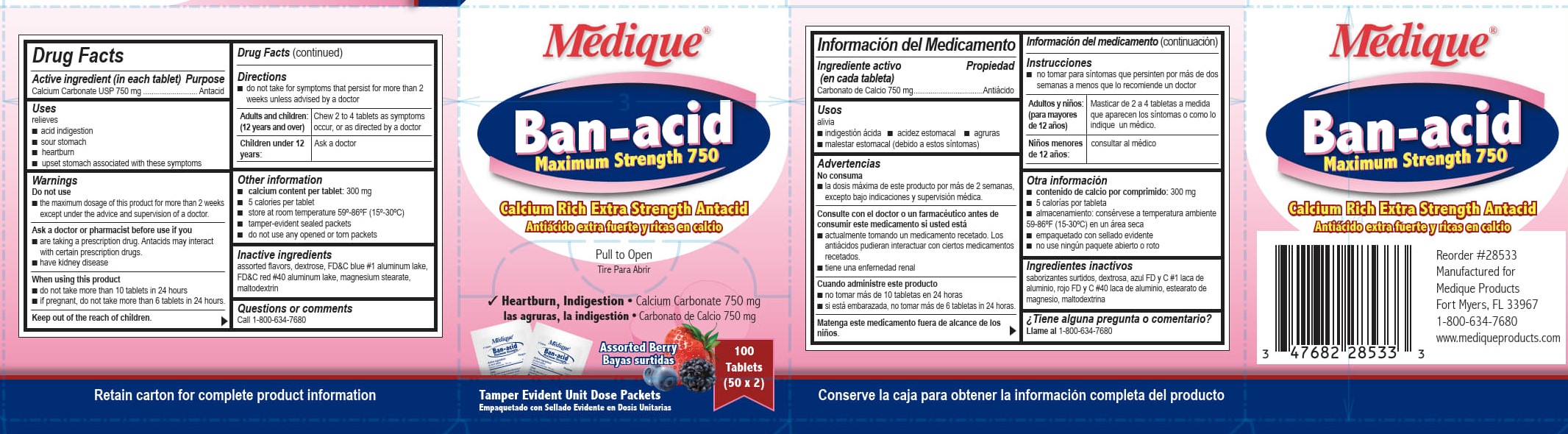 DRUG LABEL: Medique Ban-acid
NDC: 47682-285 | Form: TABLET, CHEWABLE
Manufacturer: Unifirst First Aid Corporation
Category: otc | Type: HUMAN OTC DRUG LABEL
Date: 20250908

ACTIVE INGREDIENTS: CALCIUM CARBONATE 750 mg/1 1
INACTIVE INGREDIENTS: DEXTROSE; FD&C BLUE NO. 1; FD&C RED NO. 40; MAGNESIUM STEARATE; MALTODEXTRIN

Medique Ban-Acid

Drug Facts

Active ingredient (in each tablet)

Calcium Carbonate USP 750 mg

Purpose

Antacid

Uses

relieves

- acid indigestion
- sour stomach
- heartburn
- upset stomach associated with these symptoms

Warnings

Do not use

■ the maximum dosage of this product for more than 2 weeks except under the advice and

supervision of a doctor

Ask a doctor or pharmacist before use if you

- are taking a prescription drug. Antacids may interact with certain prescription drugs.
- have kidney disease

When using this product

- do not take more than 10 tablets in a 24 hours
- if pregnant, do not take more than 6 tablets in 24 hours

Keep out of the reach of children.

Directions

■ do not take for symptoms that persist for more than 2 weeks unless advised by a doctor

Adults and children: (12 years and over): Chew 2 to 4 tablets as symptoms occur, or as directed by a doctor.

Children under 12 years: Ask a doctor

Other information

- calcium content per tablet: 300 mg
- 5 calories per tablet
- store at room temperature 59-86ºF (15-30ºC)
- tamper-evident sealed packets
- do not use any opened or torn packets

Inactive ingredients

assorted flavors, dextrose, FD&C blue #1 aluminum lake, FD&C red #40 aluminum lake, magnesium stearate, maltodextrinl

Questions or comments? Call 1-800-634-7680

Medique Ban-acid Label

Medique®

Ban-acid

Maximum Strength 750

Calcium Rich Extra Strength Antacid

Antiacido extra fuerte y /ricas en calcio

Pull To Open

Tire Para Abrir

√ Heartburn, Indigestion,•Calcium Carbonate 750mg

las agruras, la indigestion•Carbonato de Caldo 750mg

Assorted Berry

Bayas surtidas

100

Tablets

(50 x 2)

Tamper Evident Unit Dose Packets

Empaquetado con Sellado Evidente en Dosis Unitarias